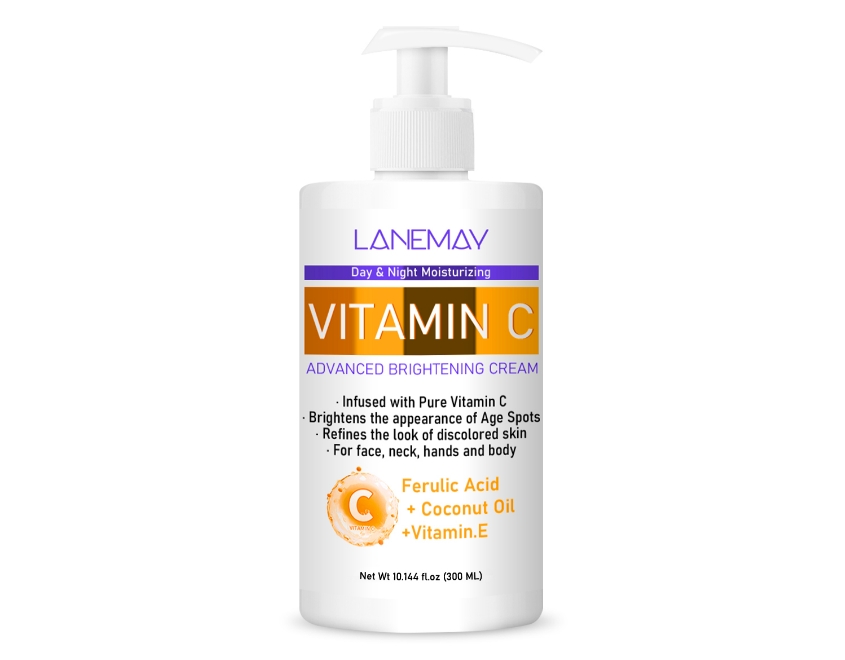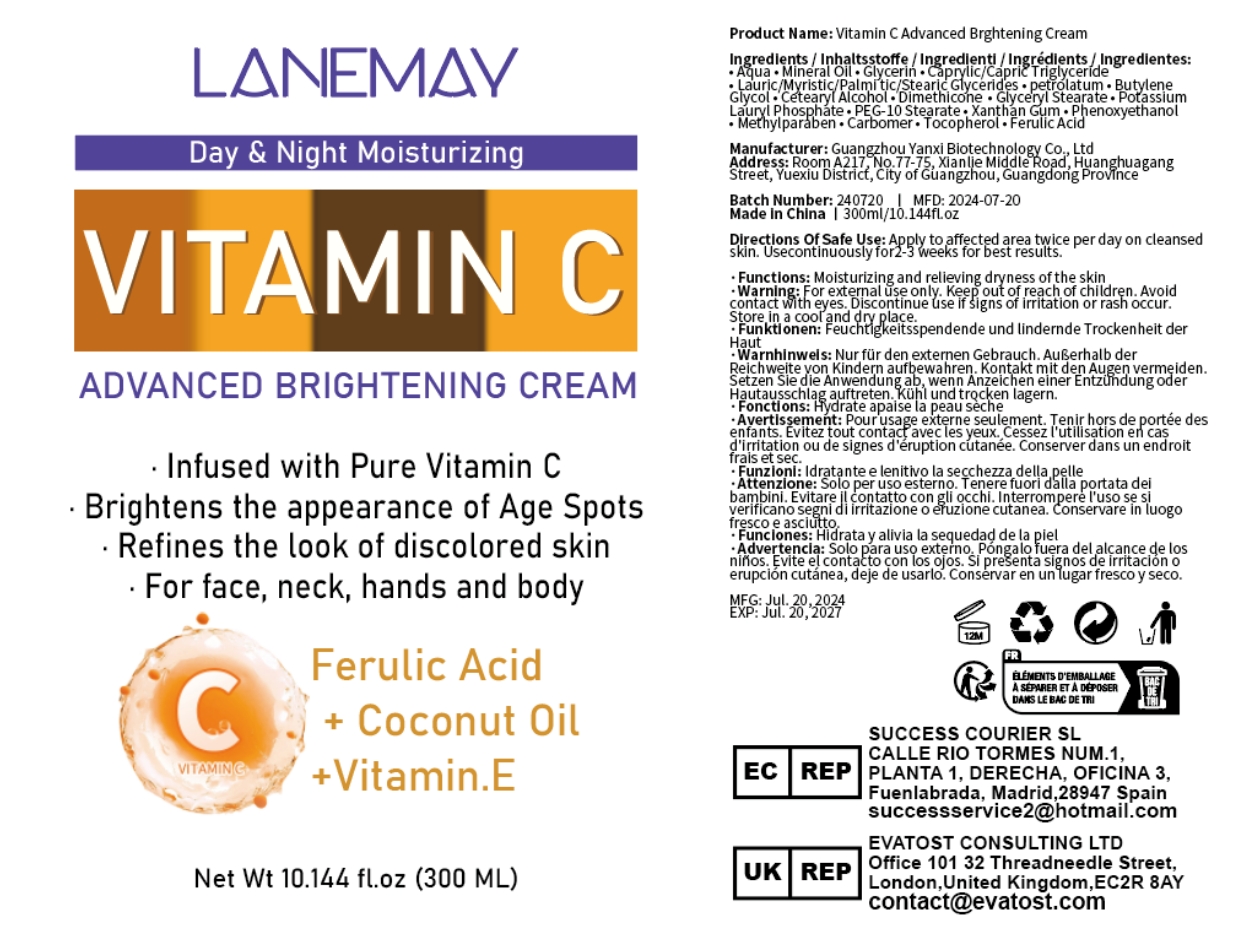 DRUG LABEL: Vitamin C Advanced Brghtening Cream
NDC: 84025-118 | Form: CREAM
Manufacturer: Guangzhou Yanxi Biotechnology Co., Ltd
Category: otc | Type: HUMAN OTC DRUG LABEL
Date: 20240805

ACTIVE INGREDIENTS: MINERAL OIL 5 mg/100 mL; GLYCERIN 3 mg/100 mL
INACTIVE INGREDIENTS: WATER

DOSAGE AND ADMINISTRATION

For face,neck, hands and body.

WARNINGS

keep out of children

INACTIVE INGREDIENT

Aqua

INDICATIONS AND USAGE

For face,neck, hands and body care.

keep out of children

PURPOSE

Infused with Pure Vitamin CBrightens the appearance of Age Spots.Refines the look of discolored skin.